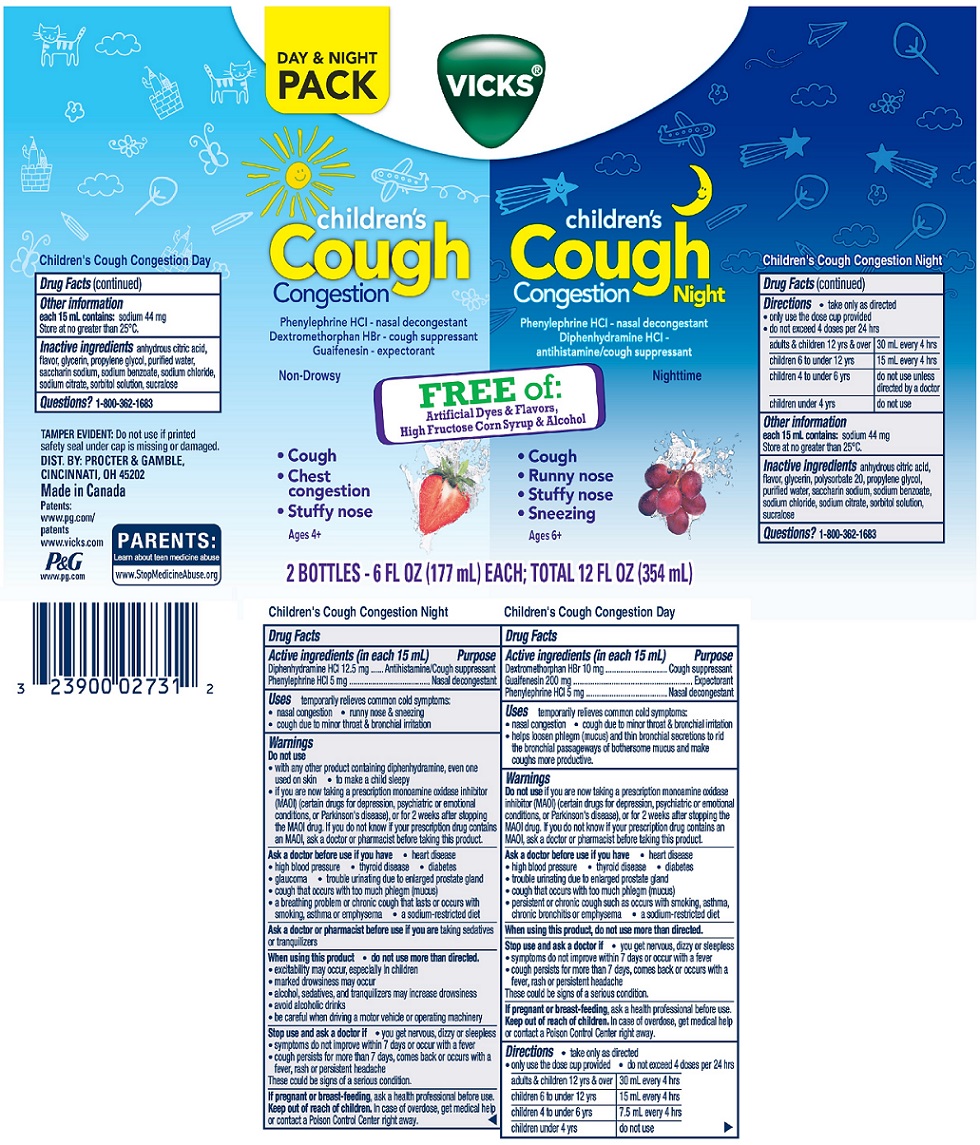 DRUG LABEL: VICKS CHILDRENS
NDC: 69423-997 | Form: KIT | Route: ORAL
Manufacturer: The Procter & Gamble Manufacturing Company
Category: otc | Type: HUMAN OTC DRUG LABEL
Date: 20251002

ACTIVE INGREDIENTS: DEXTROMETHORPHAN HYDROBROMIDE 10 mg/15 mL; GUAIFENESIN 200 mg/15 mL; PHENYLEPHRINE HYDROCHLORIDE 5 mg/15 mL; PHENYLEPHRINE HYDROCHLORIDE 5 mg/15 mL; DIPHENHYDRAMINE HYDROCHLORIDE 12.5 mg/15 mL
INACTIVE INGREDIENTS: GLYCERIN; PROPYLENE GLYCOL; WATER; SACCHARIN SODIUM; SODIUM BENZOATE; SODIUM CHLORIDE; SODIUM CITRATE; SORBITOL; SUCRALOSE; ANHYDROUS CITRIC ACID; SORBITOL; POLYSORBATE 20; WATER; SACCHARIN SODIUM; SODIUM BENZOATE; SODIUM CITRATE; GLYCERIN; SUCRALOSE; SODIUM CHLORIDE; PROPYLENE GLYCOL; ANHYDROUS CITRIC ACID

Vicks® children's Cough Congestion FREE of
Convenience Pack

Vicks children's Cough Congestion (Night)

Active ingredients (in each 15 mL)

Diphenhydramine HCl 12.5 mg

Phenylephrine HCl 5 mg

Purpose

Antihistamine/Cough suppressant
Nasal decongestant

Uses

temporarily relieves common cold symptoms:

- nasal congestion
- runny nose & sneezing
- cough due to minor throat and bronchial irritation

Warnings

Do not use

- with any other product containing diphenhydramine, even one used on skin
- to make a child sleepy
- if you are now taking a prescription monoamine oxidase inhibitor (MAOI) (certain drugs for depression, psychiatric or emotional conditions, or Parkinson's disease), or for 2 weeks after stopping the MAOI drug. If you do not know if your prescription drug contains an MAOI, ask a doctor or pharmacist before taking this product.

Ask a doctor before use if you have

- heart disease
- high blood pressure
- thyroid disease
- diabetes
- glaucoma
- trouble urinating due to enlarged prostate gland
- cough that occurs with too much phlegm (mucus)
- a breathing problem or chronic cough that lasts or as occurs with smoking, asthma, or emphysema
- a sodium-restricted diet

Ask a doctor or pharmacist before use if you are

taking sedatives or tranquilizers

When using this product

- do not use more than directed.
- excitability may occur, especially in children
- marked drowsiness may occur
- alcohol, sedatives, and tranquilizers may increase drowsiness
- avoid alcoholic drinks
- be careful when driving a motor vehicle or operating machinery

Stop use and ask a doctor if

- you get nervous, dizzy or sleepless
- symptoms do not improve within 7 days or occur with a fever
- cough persists for more than 7 days, comes back or occurs with a fever, rash or persistent headache.

These could be signs of a serious condition.

PREGNANCY OR BREAST FEEDING

If pregnant or breast-feeding,ask a health professional before use.

Keep out of reach of children.

In case of overdose, get medical help or contact a Poison Control Center right away.

Directions

- take only as directed
- only use the dose cup provided
- do not exceed 4 doses per 24 hrs

adults & children 12 yrs & over | 30 mL every 4 hrs
children 6 to under 12 yrs | 15 mL every 4 hrs
children 4 to under 6 yrs | do not use unless directed by a doctor
children under 4 yrs | do not use

Other information

- each 15 mL contains:sodium 44 mg
- Store at no greater than 25ºC.

Inactive ingredients

anhydrous citric acid, flavor, glycerin, polysorbate 20, propylene glycol, purified water, saccharin sodium, sodium benzoate, sodium chloride, sodium citrate, sorbitol solution, sucralose

Questions?

1-800-362-1683

DIST. BY: PROCTER & GAMBLE, CINCINNATI, OH 45202

Made in Canada

VICKS® childrens Cough Congestion(Day)

Active ingredients (in each 15 mL)

Dextromethorphan HBr 10 mg

Guaifenesin 200 mg

Phenylephrine HCl 5 mg

Purpose

Cough suppressant
Expectorant

Nasal decongestant

Uses

temporarily relieves common cold symptoms:

- nasal congestion
- cough due to minor throat and bronchial irritation
- helps loosen phlegm (mucus) and thin bronchial secretions to rid the bronchial passageways of bothersome mucus and make coughs more productive.

Warnings

Do not use

if you are now taking a prescription monoamine oxidase inhibitor (MAOI) (certain drugs for depression, psychiatric or emotional conditions, or Parkinson's disease), or for 2 weeks after stopping the MAOI drug. If you do not know if your prescription drug contains an MAOI, ask a doctor or pharmacist before taking this product.

Ask a doctor before use if you have

- heart disease
- high blood pressure
- thyroid disease
- diabetes
- trouble urinating due to enlarged prostate gland
- cough that occurs with too much phlegm (mucus)
- persistent or chronic cough such as occurs with smoking, asthma, chronic bronchitis or emphysema
- a sodium-restricted diet

When using this product, do not use more than directed.

Stop use and ask a doctor if

- you get nervous, dizzy or sleepless
- symptoms do not improve within 7 days or occur with a fever
- cough persists for more than 7 days, comes back or occurs with a fever, rash or persistent headache

These could be signs of a serious condition.

PREGNANCY OR BREAST FEEDING

If pregnant or breast-feeding,ask a health professional before use.

Keep out of reach of children.

Directions

- take only as directed
- only use the dose cup provided
- do not exceed 4 doses per 24 hrs

adults & children 12 yrs & over | 30 mL every 4 hrs
children 6 to under 12 yrs | 15 mL every 4 hrs
children 4 to under 6 yrs | ask a doctor
children under 4 yrs | do not use

Other information

- each 15 mL contains: sodium 44 mg
- store at no greater than 25ºC

Inactive ingredients

anhydrous citric acid, flavor, glycerin, propylene glycol, purified water, saccharin sodium, sodium benzoate, sodium chloride, sodium citrate, sorbitol solution, sucralose

Questions?

1-800-362-1683

TAMPER EVIDENT: Do not use if printed safety seal under cap is missing or damaged

DIST. BY: PROCTER & GAMBLE, CINCINNATI, OH 45202

Made in Canada

PRINCIPAL DISPLAY PANEL - Kit Carton

DAY & NIGHT PACK

children's Cough Congestion

Phenylephrine HCl - nasal decongestant

Dextromethorphan HBr - cough suppressant

Guaifenesin - expectorant

Non-Drowsy

FREE of:

Artificial Dyes & Flavors,

High Fructose Corn Syrup & Alcohol

- Cough
- Chest congestion
- Stuffy nose

Ages 4+

children's Cough Congestion Night

Phenylephrine HCl - nasal decongestant

Diphenhydramine HCl - antihistamine/cough suppressant

Nighttime

FREE of:

Artificial Dyes & Flavors,

High Fructose Corn Syrup & Alcohol

- Cough
- Runny nose
- Stuffy nose
- Sneezing

Ages 6+

2 BOTTLES - 6 FL OZ (177 mL) EACH; TOTAL 12 FL OZ (354 mL)